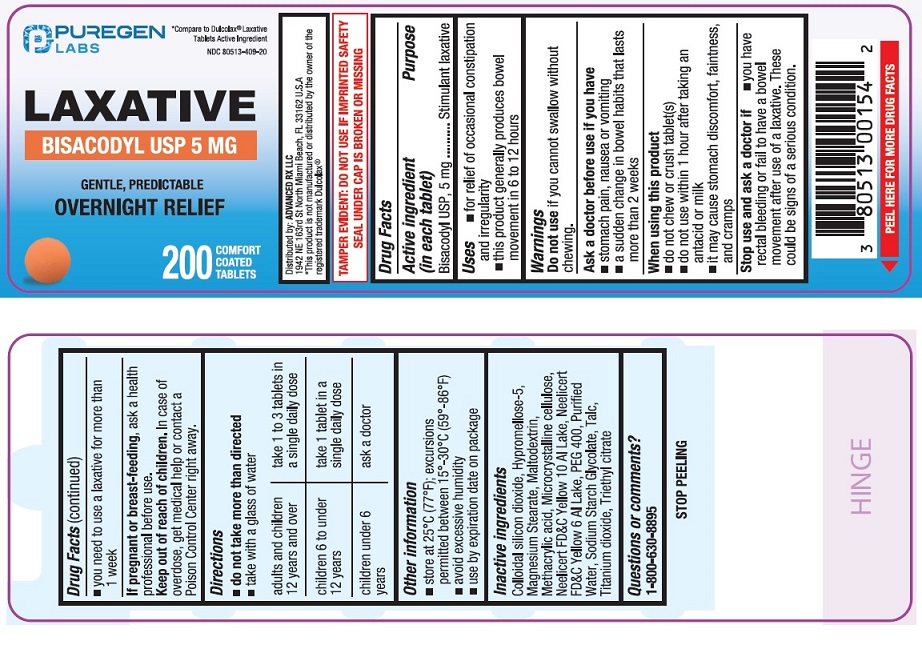 DRUG LABEL: Laxative
NDC: 80513-409 | Form: TABLET, DELAYED RELEASE
Manufacturer: Advanced Rx LLC
Category: otc | Type: HUMAN OTC DRUG LABEL
Date: 20250122

ACTIVE INGREDIENTS: BISACODYL 5 mg/1 1
INACTIVE INGREDIENTS: SILICON DIOXIDE; HYPROMELLOSE 2910 (5 MPA.S); MAGNESIUM STEARATE; MALTODEXTRIN; METHACRYLIC ACID; CELLULOSE, MICROCRYSTALLINE; D&C YELLOW NO. 10 ALUMINUM LAKE; FD&C YELLOW NO. 6 ALUMINUM LAKE; POLYETHYLENE GLYCOL 400; WATER; SODIUM STARCH GLYCOLATE TYPE A; TALC; TITANIUM DIOXIDE; TRIETHYL CITRATE

Active ingredient (in each tablet)

Bisacodyl USP, 5 mg

Purpose

Stimulant laxative

Uses

- for relief of occasional constipation and irregularity
- this product generally produces bowel movement in 6 to 12 hours

Warnings

Do not use

if you cannot swallow without chewing.

Ask a doctor before use if you have

- stomach pain, nausea or vomiting
- a sudden change in bowel habits that lasts more than 2 weeks

When using this product

- do not chew or crush tablet(s)
- do not use within 1 hour after taking an antacid or milk
- it may cause stomach discomfort, faintness, and cramps

Stop use and ask a doctor if

- you have rectal bleeding or fail to have a bowel movement after use of a laxative. These could be signs of a serious condition.
- you need to use a laxative for more than 1 week

If pregnant or breast-feeding,

ask a health professional before use.

Keep out of reach of children.

In case of overdose, get medical help or contact a Poison Control Center right away.

Directions

- do not take more than directed
- take with a glass of water

adults and children 12 years and over | take 1 to 3 tablets in a single daily dose
children 6 to under 12 years | take 1 tablet in a single daily dose
children under 6 years | ask a doctor

Other information

- TAMPER EVIDENT: DO NOT USE IF IMPRINTED SAFETY SEAL UNDER CAP IS BROKEN OR MISSING
- store at 25°C (77°F); excursions permitted between 15°-30°C (59°-86°F)
- avoid excessive humidity
- use by expiration date on package

Inactive ingredients

Colloidal silicon dioxide, Hypromellose-5, Magnesium stearate, Maltodextrin, Methacrylic acid, Microcrystalline cellulose, Neelicert FD&C Yellow 10 Al Lake, Neelicert FD&C Yellow 6 Al Lake, PEG 400, Purified Water, Sodium Starch Glycolate, Talc, Titanium Dioxide, Triethyl citrate.

Questions or comments?

1-800-630-8895

Distributed by

ADVANCED RX LLC

1942 NE 163rd St.North Miami Beach,

FL 33162 U.S.A.

PACKAGE LABEL

NDC 80513-409-20

*Compare to Dulcolax ® Laxative Tablets Active Ingredient

Laxative

Bisacodyl USP 5 mg

Gentle Predictable

Overnight Relief

200 Comfort Coated Tablets

*This product is not manufactured or distributed by the owner of the registered trademark Dulcolax ®.